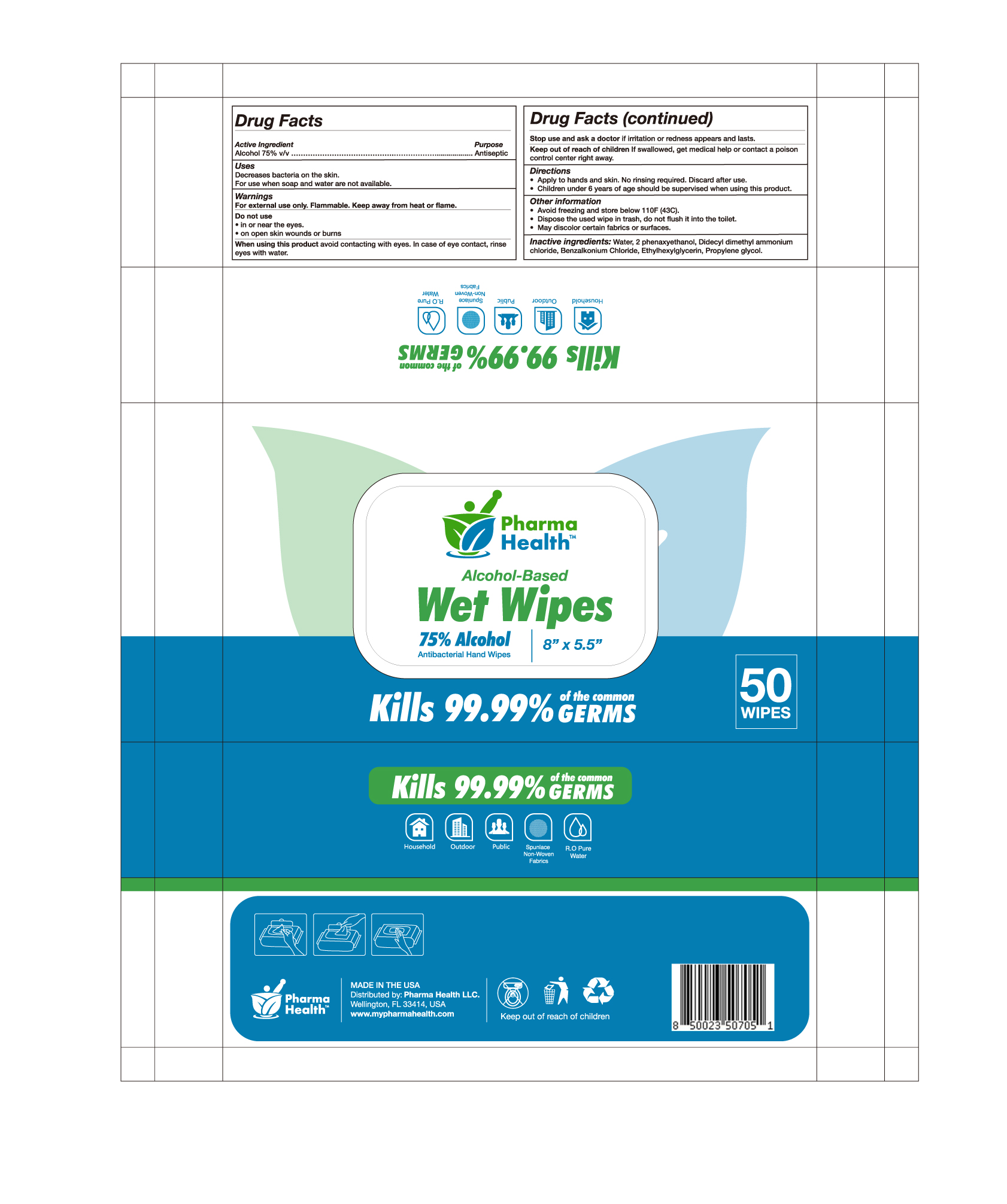 DRUG LABEL: Pharma Health
NDC: 79040-122 | Form: CLOTH
Manufacturer: Pharma Health LLC
Category: otc | Type: HUMAN OTC DRUG LABEL
Date: 20201002

ACTIVE INGREDIENTS: ALCOHOL 0.75 mL/1 1
INACTIVE INGREDIENTS: BENZALKONIUM CHLORIDE; PROPYLENE GLYCOL; GLYCERIN; PHENOXYETHANOL; WATER; DIDECYLDIMONIUM CHLORIDE

Pharma Cleanse Wipe 50 PCS TEST

Active Ingredient(s)

Alcohol 75% v/v. Purpose: Antiseptic

Purpose

Antiseptic

Use

For sanitizing and to help reduce bacteria on the skin. For use when soap and water are not available.

Warnings

For external use only. Flammable. Keep away from heat or flame

Do not use

- in children less than 2 months of age
- on open skin wounds

When using this product keep out of eyes, ears, and mouth. In case of contact with eyes, rinse eyes thoroughly with water.
Stop use and ask a doctor if irritation or rash occurs. These may be signs of a serious condition.
Keep out of reach of children. If swallowed, get medical help or contact a Poison Control Center right away.

Stop use and ask a doctor if irritation or rash occurs. These may be signs of a serious condition.

Keep out of reach of children. If swallowed, get medical help or contact a Poison Control Center right away.

Directions

Apply to hands and skin. No rinsing required. Discard after use.

Children under 6 years of age should be supervised when using this product.

Other information

Avoid freezing and store below 110F (43C).
Dispose the used wipe in trash, do not flush it into the toilet.

May discolor certain fabrics or surfaces.

Inactive ingredients

2 phenaxythanol, benzalkonium chloride, didecyl dimethyl ammonium, ethylhexylglycerin, propylene glycol, water

Package Label - Principal Display Panel

50 PCS NDC: 79040-122-01